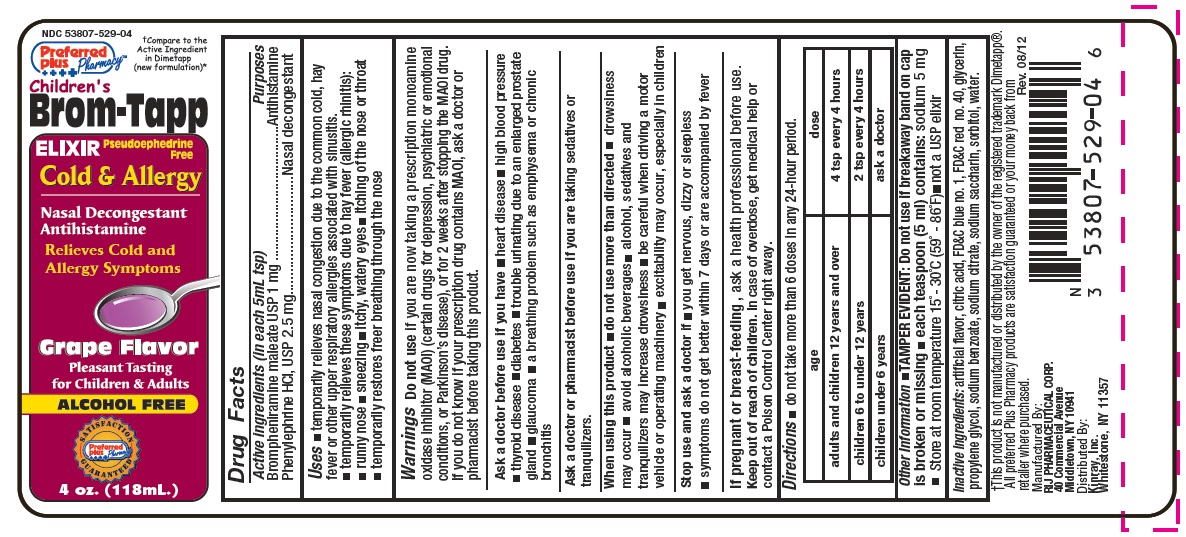 DRUG LABEL: Brom Tapp
NDC: 53807-529 | Form: LIQUID
Manufacturer: Rij Pharmaceutical Corporation
Category: otc | Type: HUMAN OTC DRUG LABEL
Date: 20180430

ACTIVE INGREDIENTS: BROMPHENIRAMINE MALEATE 1 mg/5 mL; PHENYLEPHRINE HYDROCHLORIDE 2.5 mg/5 mL
INACTIVE INGREDIENTS: ANHYDROUS CITRIC ACID; FD&C BLUE NO. 1; FD&C RED NO. 40; GLYCERIN; PROPYLENE GLYCOL; WATER; SODIUM BENZOATE; SODIUM CITRATE; SORBITOL; SACCHARIN SODIUM

Drug Facts

Active Ingredients (in each 5mL tsp)

Brompheniramine maleate, USP 1 mg

Phenylephrine HCl , USP 2.5 mg

PURPOSES

Antihistamine

Nasal decongestant

USES

- temporarily relieves nasal congestion due to the common cold, hay fever or other upper respiratory allergies associated with sinusitis
- temporarily relieves these symptoms due to hay fever (allergic rhinitis):
  - runny nose
  - sneezing
  - itchy, watery eyes
  - itching of the nose or throat

- temporarily restores freer breathing through the nose

WARNINGS

Do not use

- if you are now taking a prescription monoamine oxidase inhibitor (MAOI) (certain drugs for depression, psychiatric, or emotional conditions, or Parkinson's disease), or for 2 weeks after stopping the MAOI drug. If you do not know if your prescription drug contains MAOI, ask a doctor or pharmacist before taking this product.

Ask a doctor before use if you have

- heart disease
- high blood pressure
- thyroid disease
- diabetes
- trouble urinating due to an enlarged prostate gland
- glaucoma
- a breathing problem such as emphysema, or chronic bronchitis

Ask a doctor or pharmacist before use if you are

- taking sedatives or tranquilizers

When using this product

- do not use more than directed
- drowsiness may occur
- avoid alcoholic beverages
- alcohol, sedatives, and tranquilizers may increase drowsiness
- be careful when driving a motor vehicle or operating machinery
- excitability may occur, especially in children

Stop use and ask a doctor if

- you get nervous, dizzy, or sleepless
- symptoms do not get better within 7 days or are accompanied by fever

If pregnant or breast-feeding,

ask a health professional before use.

Keep out of reach of children.

In case of overdose, get medical help or contact a Poison Control Center right away.

DIRECTIONS

- do not take more than 6 doses in any 24-hour period

age | dose
adults and children 12 years and over | 4 tsp every 4 hours
children 6 to under 12 years | 2 tsp every 4 hours
children under 6 years | ask a doctor

Other Information

- TAMPER EVIDENT: Do not use if breakaway band on cap is broken or missing
- each teaspoon (5 ml) contains: sodium 5 mg
- store at room temperature 15º - 30ºC (59º - 86ºF)
- not a USP elixir

INACTIVE INGREDIENTS

artificial flavor, citric acid, FD&C blue no. 1, FD&C red no. 40, glycerin, propylene glycol, sodium benzoate, sodium citrate, sodium saccharin, sorbitol, water